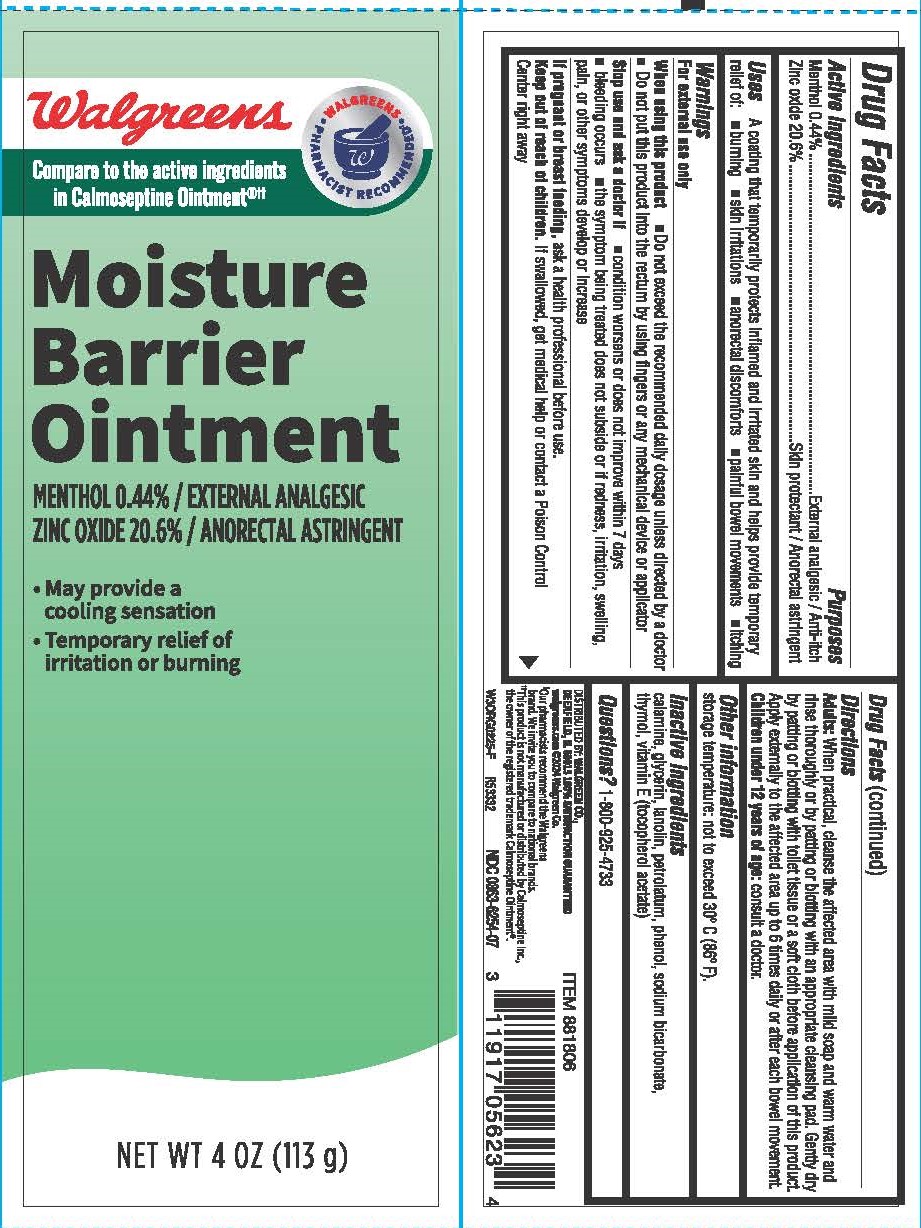 DRUG LABEL: Moisture Barrier
NDC: 0363-6254 | Form: OINTMENT
Manufacturer: Walgreen Company
Category: otc | Type: HUMAN OTC DRUG LABEL
Date: 20251031

ACTIVE INGREDIENTS: ZINC OXIDE 20.6 g/100 g; MENTHOL 0.44 g/100 g
INACTIVE INGREDIENTS: FERRIC OXIDE RED; PHENOL; GLYCERIN; LANOLIN; PETROLATUM; THYMOL; ALPHA-TOCOPHEROL ACETATE; SODIUM BICARBONATE

6254- Walgreen

Drug Facts

Active ingredients

Menthol 0.44%

Zinc oxide 20.6%

Purposes

External analgesic / Anti-itch

Skin protectant / Anorectal astringent

Uses

A coating that temporarily protects inflamed and irritated skin and helps provide temporary relief of:

- burning
- skin irritations
- anorectal discomforts
- painful bowel movements
- itching

Warnings

For external use only

When using this product

- Do not exceed the recommended daily dosage unless directed by a doctor
- Do not put this product into the rectum by using fingers or any mechanical device or applicator

Stop use and ask a doctor if

- condition worsens or does not improve within 7 days
- bleeding occurs
- the symptom being treated does not subside or if redness, irritation, swelling, pain, or other symptoms develop or increase

PREGNANCY OR BREAST FEEDING

If pregnant or breast feeding, ask a health professional before use.

Keep out of reach of children.

OVERDOSAGE

If swallowed, get medical help or contact a Poison Control Center right away

Directions

Adults: When practical, cleanse the affected area with mild soap and warm water and rinse thoroughly or by patting or blotting with an appropriate cleansing pad. Gently dry by patting or blotting with toilet tissue or a soft cloth before application of this product. Apply externally to the affected area up to 6 times daily or after each bowel movement.

Children under 12 years of age: consult a doctor.

Other information

storage temperature: not to exceed 30° C (86° F).

Inactive ingredients

calamine, glycerin, lanolin, petrolatum, phenol, sodium bicarbonate, thymol, vitamin E (tocopherol acetate)

Questions?

1-800-925-4733

DISTRIBUTED BY: WALGREEN CO.,

DEERFIELD, IL 60015 100% SATISFACTION GUARANTEED

walgreens.com ©2024 Walgreen Co.

†Our pharmacists recommend the Walgreens brand. We invite you to compare to national brands.

††This product is not manufactured or distributed by Calmoseptine Inc., the owner of the registered trademark Calmoseptine Ointment®.

NDC 0363-6254-07

PACKAGE LABEL

Walgreens

Walgreens Pharmacist Recommended†

Compare to the active ingredients in Calmoseptine Ointment®††

Moisture Barrier Ointment

MENTHOL 0.44% / EXTERNAL ANALGESIC

ZINC OXIDE 20.6% / ANORECTAL ASTRINGENT

- May provide a cooling sensation
- Temporary relief of irritation or burning

NET WT 4 OZ (113 g)